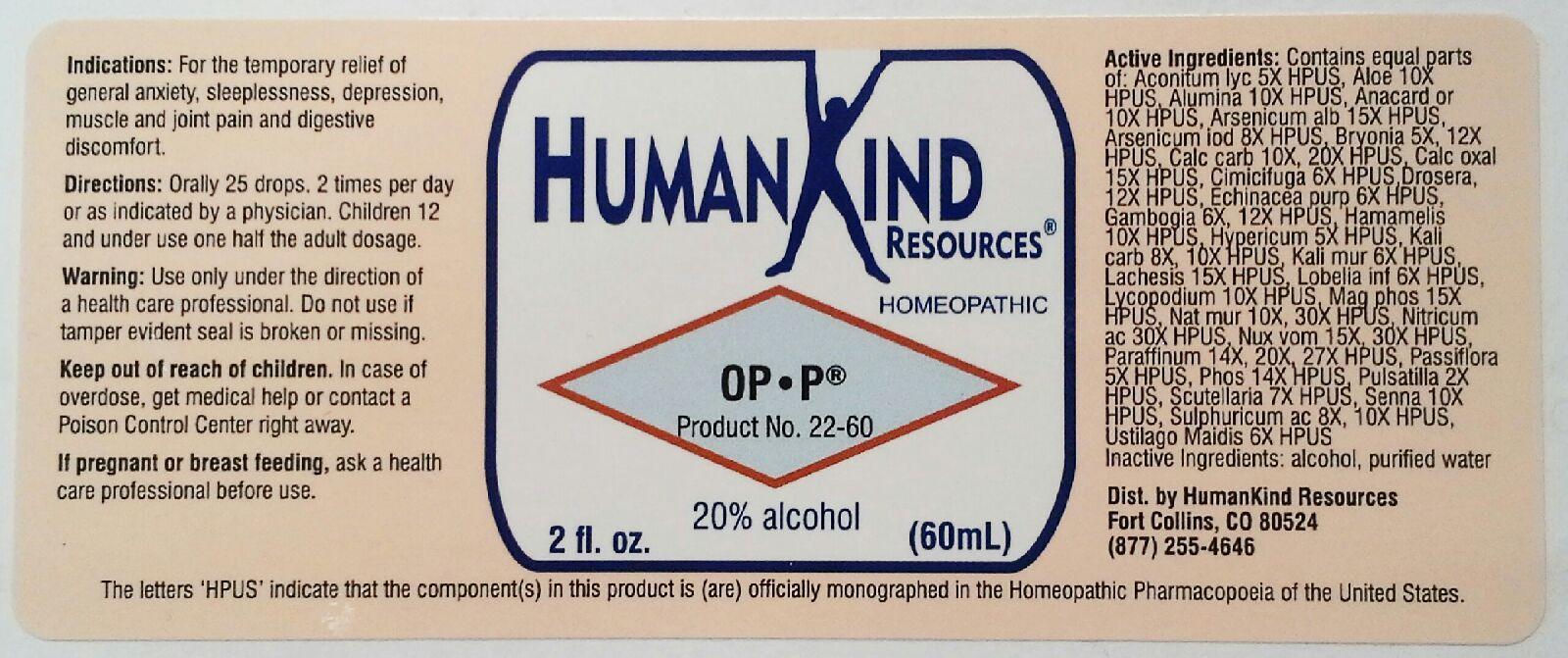 DRUG LABEL: OP-P
NDC: 64616-100 | Form: LIQUID
Manufacturer: Vitality Works, Inc.
Category: homeopathic | Type: HUMAN OTC DRUG LABEL
Date: 20251217

ACTIVE INGREDIENTS: ARSENIC TRIIODIDE 8 [hp_X]/1 mL; BRYONIA ALBA ROOT 12 [hp_X]/1 mL; OYSTER SHELL CALCIUM CARBONATE, CRUDE 12 [hp_X]/1 mL; CALCIUM OXALATE MONOHYDRATE 15 [hp_X]/1 mL; BLACK COHOSH 6 [hp_X]/1 mL; DROSERA ROTUNDIFOLIA 12 [hp_X]/1 mL; ECHINACEA PURPUREA 6 [hp_X]/1 mL; GAMBOGE 12 [hp_X]/1 mL; HAMAMELIS VIRGINIANA ROOT BARK/STEM BARK 10 [hp_X]/1 mL; HYPERICUM PERFORATUM 5 [hp_X]/1 mL; POTASSIUM CARBONATE 10 [hp_X]/1 mL; POTASSIUM CHLORIDE 6 [hp_X]/1 mL; LACHESIS MUTA VENOM 15 [hp_X]/1 mL; LOBELIA INFLATA 6 [hp_X]/1 mL; LYCOPODIUM CLAVATUM SPORE 10 [hp_X]/1 mL; MAGNESIUM PHOSPHATE, DIBASIC TRIHYDRATE 15 [hp_X]/1 mL; SODIUM CHLORIDE 30 [hp_X]/1 mL; NITRIC ACID 30 [hp_X]/1 mL; STRYCHNOS NUX-VOMICA SEED 30 [hp_X]/1 mL; PARAFFIN 27 [hp_X]/1 mL; PASSIFLORA INCARNATA FLOWERING TOP 5 [hp_X]/1 mL; PHOSPHORUS 14 [hp_X]/1 mL; PULSATILLA PRATENSIS 2 [hp_X]/1 mL; SCUTELLARIA LATERIFLORA 7 [hp_X]/1 mL; SENNA LEAF 10 [hp_X]/1 mL; SULFURIC ACID 10 [hp_X]/1 mL; USTILAGO MAYDIS 6 [hp_X]/1 mL; ACONITUM LYCOCTONUM 5 [hp_X]/1 mL; ALOE 10 [hp_X]/1 mL; ALUMINUM OXIDE 10 [hp_X]/1 mL; SEMECARPUS ANACARDIUM JUICE 10 [hp_X]/1 mL; ARSENIC TRIOXIDE 15 [hp_Q]/1 mL
INACTIVE INGREDIENTS: ALCOHOL; WATER

OP-P

OP-P

Aconitum Lycoctonum 5X Echinacea Purpurea 6X Nitricum Acidum 30X

Aloe Socotrina 10X Gambogia 6X, 12X Nux Vomica 15X, 30X

Alumina 10X Hamamelis Virginiana 10X Paraffinum 14X, 20X, 27X

Anacardium Orientale 10X Hypericum Perforatum 5X Passiflora Incarnata 5X

Aresenicum Album 15X Kali Carbonicum 8X, 10X Phosphorus 14X

Arsenicum Iodatum 8X Kali Muriaticum 6X Pulsatilla Nigricans 2X

Bryonia Alba 5X, 12X Lachesis Mutus 15X Scutellaria Lateriflora 7X

Calcarea Carbonica 10X, 12X Lobelia Inflata 6X Senna 10X

Calcarea Oxalica 15X Lycopodium Clavatum 10X Sulphuricum Acidum 8X, 10X

Cimicifuga Racemosa 6X Magnesia Phosphorica 15X Ustilago Maidis 6X

Drosera Rotundifolia 12X Natrum Muriaticum 10X, 30X

OP-P

Alcohol, Purified Water

OP-P

Use only under the direction of a health care professional. Do not use if tamper evident seal is broken or missing.

OP-P

Keep out of reach of children. In case of overdose, get medical help or contact a Poison Control Center right away.

OP-P

For the temporary relief of general anxiety, sleeplessness, depression, muscle and joint pain and digestive discomfort

OP-P

Orally 25 drops, 2 times per day or as indicated by a physician. Children 12 and under use one half the adult dosage.

OP-P

Aids in emotional health by balancing bio-chemical, nutritional and structural functions.